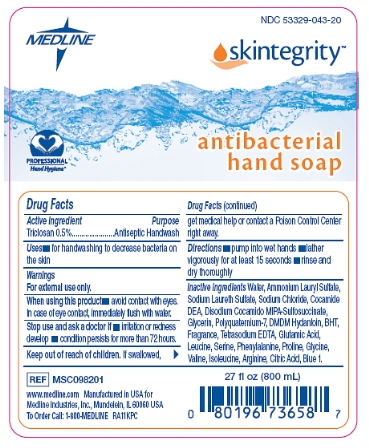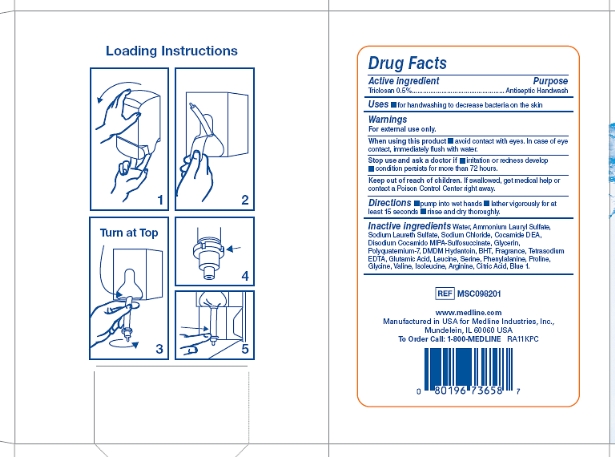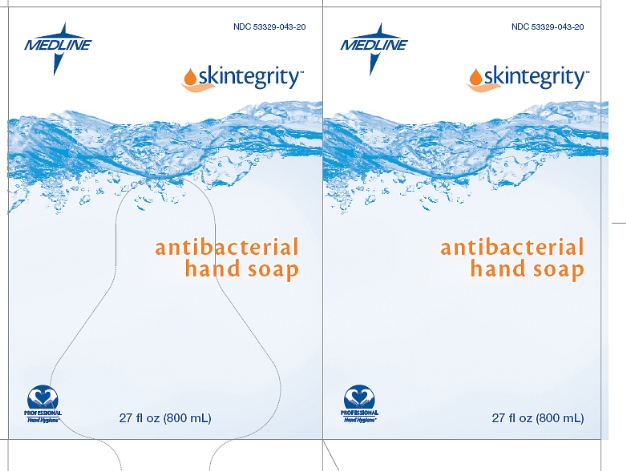 DRUG LABEL: Skintegrity Antibacterial Hand
NDC: 53329-043 | Form: SOAP
Manufacturer: Medline Industries, Inc.
Category: otc | Type: HUMAN OTC DRUG LABEL
Date: 20110713

ACTIVE INGREDIENTS: TRICLOSAN 0.5 mL/100 mL
INACTIVE INGREDIENTS: WATER; AMMONIUM LAURYL SULFATE; SODIUM LAURETH SULFATE; SODIUM CHLORIDE; COCO DIETHANOLAMIDE; GLYCERIN; POLYQUATERNIUM-7 (70/30 ACRYLAMIDE/DADMAC; 1600 KD); DMDM HYDANTOIN; BUTYLATED HYDROXYTOLUENE; EDETATE SODIUM; GLUTAMIC ACID; LEUCINE; SERINE; PHENYLALANINE; PROLINE; GLYCINE; VALINE; ISOLEUCINE; ARGININE; CITRIC ACID MONOHYDRATE; FD&C BLUE NO. 1

Drug Facts

Active ingredient

Triclosan 0.5%

Purpose

Antiseptic Handwash

Uses

- for handwashing to decrease bacteria on the skin

Warnings

For external use only.

When using this product

- avoid contact with eyes. In case of eye contact, immediately flush with water.

Stop use and ask a doctor if

- irritation or redness develop
- condition persists for more than 72 hours.

Keep out of reach of children.

If swallowed, get medical help or contact a Poison Control Center right away.

Directions

- pump into wet hands
- lather vigorously for at least 15 seconds
- rinse and dry thoroughly

Inactive ingredients

Water, Ammonium Lauryl Sulfate, Sodium Laureth Sulfate, Sodium Chloride, Cocamide DEA, Disodium Cocamido MIPA-Sulfosuccinate, Glycerin, Polyquaternium-7, DMDM Hydantoin, BHT, Fragrance, Tetrasodium EDTA, Glutamic Acid, Leucine, Serine, Phenylalanine, Proline, Glycine, Valine, Isoleucine, Arginine, Citric Acid, Blue 1.

Package/Label Principal Display Panel

Skintegrity Antibacterial Hand Soap bag label

NDC 53329-043-20

skintegrity

antibacterial hand soap

27 fl oz (800 mL)

Package Box Label - Back and Side

Skintegrity Antibacterial Hand Soap box, back and side

Package Box Label - Front and side

Skintegrity Antibacterial Hand Soap box, front and side